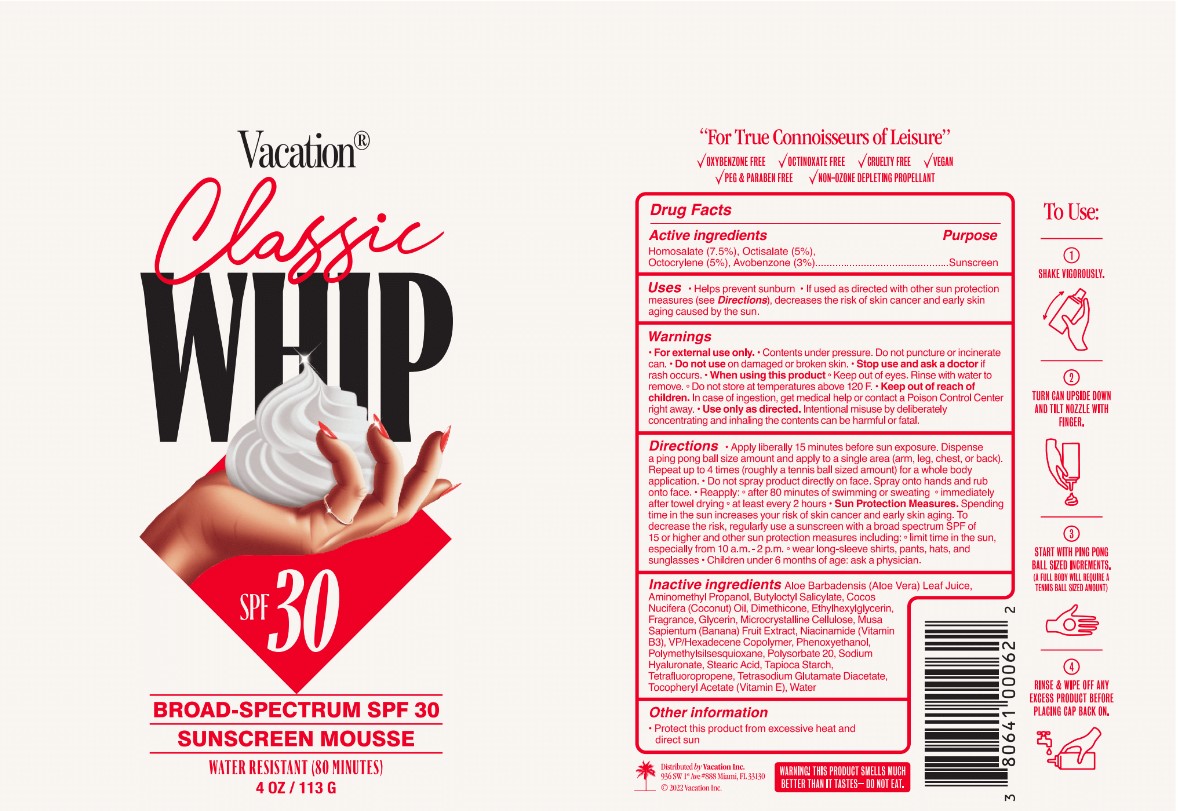 DRUG LABEL: Vacation World
NDC: 80641-005 | Form: AEROSOL, FOAM
Manufacturer: Vacation Inc.
Category: otc | Type: HUMAN OTC DRUG LABEL
Date: 20241023

ACTIVE INGREDIENTS: OCTISALATE 0.05 g/1 g; HOMOSALATE 0.075 g/1 g; OCTOCRYLENE 0.05 g/1 g; AVOBENZONE 0.03 g/1 g
INACTIVE INGREDIENTS: 1,3,3,3-TETRAFLUOROPROPENE, (1E)-; POLYMETHYLSILSESQUIOXANE (4.5 MICRONS); GLYCERIN; POLYSORBATE 20; VINYLPYRROLIDONE/HEXADECENE COPOLYMER; COCONUT OIL; AMINOMETHYLPROPANOL; ETHYLHEXYLGLYCERIN; MICROCRYSTALLINE CELLULOSE; NIACINAMIDE; ALOE VERA LEAF; BUTYLOCTYL SALICYLATE; STARCH, TAPIOCA; TETRASODIUM GLUTAMATE DIACETATE; ALPHA-TOCOPHEROL ACETATE; WATER; DIMETHICONE; BANANA; HYALURONATE SODIUM; STEARIC ACID; PHENOXYETHANOL

Vacation Classic Whip Broad Spectrum SPF 30 Sunscreen Mousse

Active Ingredients

Homosalate 7.5%, Octisalate 5%, Octocrylene 5%, Avobenzone 3%

Purpose

Sunscreen

Uses

- Helps prevent sunburn
- If used as directed with other sun protection measures (see Directions), decreases the risk of skin cancer and early skin aging caused by the sun.

Warnings

- For external use only
- Contents under pressure. Do not puncture or incinerate can.

Do not use on damaged or broken skin.

Stop use and ask a doctor if rash occurs

When using this product

- Keep out fo eyes. Rinse with water to remove.
- Do not store at temperatures above 120 F.

- Keep out of reach of children. In case of ingestiion, get medical help or contact a Poison Control Center right away.

WHEN USING

Use only as directed. intentional misuse by deliberately concentrating and inhaling the contents can be harmful or fatal.

Directions

- Apply liberally 15 minutes before sun exposure. Dispense a ping pong ball size amount and apply to a single area (arm,leg,chest,or back). Repeat up to 4 times (roughly a tennis ball size amount) for a whole body application.
- Do not spray product directly on face. Spray onto hands and rub onto face.
- Reapply:
- after 80 minutes of swimming or sweating
- immediately after towel drying
- at least every 2 hours
- Sun Protection Measures. Spending time in the sun increases your risk of skin cancer and early skin aging. To decrease the risk, regularly use a sunscreen with a broad spectrum SPF of 15 or higher and other sun protection measures including
- limit time in the sun, especially from 10 a.m.- 2 p.m.
- wear long-sleeve shirts, pants, hats, and sunglasses
- Chidlren under 6 months of age: ask a physician

Inactive Ingredients

Aloe Barbadensis (Aloe Vera) Leaf Juice, Aminomethyl Propanol, Butyloctyl Salicylate, Cocos Nucifera (Coconut) Oil, Dimethicone, Ethylhexylglycerin, Fragrance, Glycerin, Microcrystalline Cellulose, Musa Sapientum (Banana) Fruit Extract, Niacinamide (Vitamin B3), VP/Hexadecene Copolymer, Phenoxyethanol, Polymethylsilsesquioxane, Polysorbate 20, Sodium Hyaluronate, Stearic Acid, Tapioca Starch, Tetrafluoropropene, Tetrasodium Glutamate Diacetate , Tocopheryl Acetate (Vitamin E), Water

Other information

- Protect this product from excessive heat and direct sun